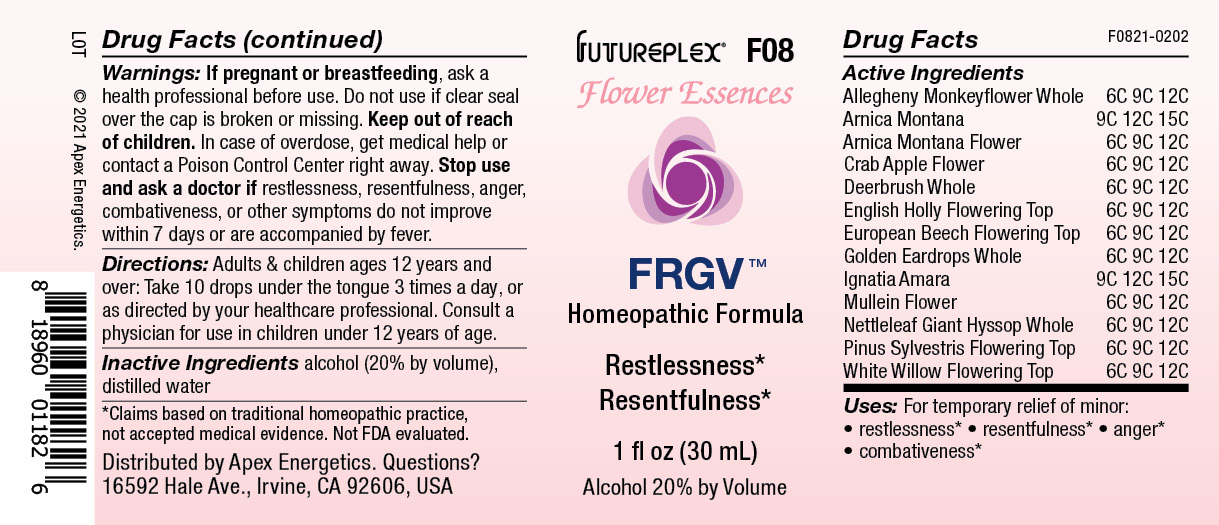 DRUG LABEL: F08
NDC: 63479-0608 | Form: SOLUTION/ DROPS
Manufacturer: Apex Energetics Inc.
Category: homeopathic | Type: HUMAN OTC DRUG LABEL
Date: 20240108

ACTIVE INGREDIENTS: PINUS SYLVESTRIS FLOWERING TOP 12 [hp_C]/1 mL; SALIX ALBA FLOWERING TOP 12 [hp_C]/1 mL; STRYCHNOS IGNATII SEED 15 [hp_C]/1 mL; VERBASCUM DENSIFLORUM FLOWER 12 [hp_C]/1 mL; AGASTACHE URTICIFOLIA WHOLE 12 [hp_C]/1 mL; MIMULUS RINGENS WHOLE 12 [hp_C]/1 mL; MALUS SYLVESTRIS FLOWER 12 [hp_C]/1 mL; ARNICA MONTANA 15 [hp_C]/1 mL; ARNICA MONTANA FLOWER 12 [hp_C]/1 mL; CEANOTHUS INTEGERRIMUS WHOLE 12 [hp_C]/1 mL; ILEX AQUIFOLIUM FLOWERING TOP 12 [hp_C]/1 mL; FAGUS SYLVATICA FLOWERING TOP 12 [hp_C]/1 mL; EHRENDORFERIA CHRYSANTHA WHOLE 12 [hp_C]/1 mL
INACTIVE INGREDIENTS: ALCOHOL; WATER

F08

Active Ingredients
Allegheny Monkeyflower Whole | 6C 9C 12C
Arnica Montana | 9C 12C 15C
Arnica Montana Flower | 6C 9C 12C
Crab Apple Flower | 6C 9C 12C
Deerbrush Whole | 6C 9C 12C
English Holly Flowering Top | 6C 9C 12C
European Beech Flowering Top | 6C 9C 12C
Golden Eardrops Whole | 6C 9C 12C
Ignatia Amara | 9C 12C 15C
Mullein Flower | 6C 9C 12C
Nettleleaf Giant Hyssop Whole | 6C 9C 12C
Pinus Sylvestris Flowering Top | 6C 9C 12C
White Willow Flowering Top | 6C 9C 12C

INDICATIONS AND USAGE

Uses:

For temporary relief of minor:

restlessness*

resentfulness*

anger*

combativeness*

*Claims based on traditional homeopathic practice, not accepted medical evidence. Not FDA evaluated.

Warnings:

PREGNANCY OR BREAST FEEDING

If pregnant or breastfeeding, ask a health professional before use.

Do not use if clear seal over the cap is broken or missing.

Keep out of reach of children. In case of overdose, get medical help or contact a Poison Control Center right away.

Stop use and ask a doctor if restlessness, resentfulness, anger, combativeness, or other symptoms do not improve within 7 days or are accompanied by fever.

Directions:

Adults & children ages 12 years and over: Take 10 drops under the tongue 3 times a day, or as directed by your healthcare professional. Consult a physician for use in children under 12 years of age.

Inactive Ingredients

alcohol (20% by volume), distilled water

PURPOSE

Distributed by Apex Energetics. Questions?

16592 Hale Ave., Irvine, CA 92606, USA

PACKAGE LABEL

FUTUREPLEX® F08

FLOWER ESSENCES

FRGV™

Homeopathic Formula

Restlessness*

Resentfulness*

1 fl oz (30 mL)

Alcohol 20% by Volume